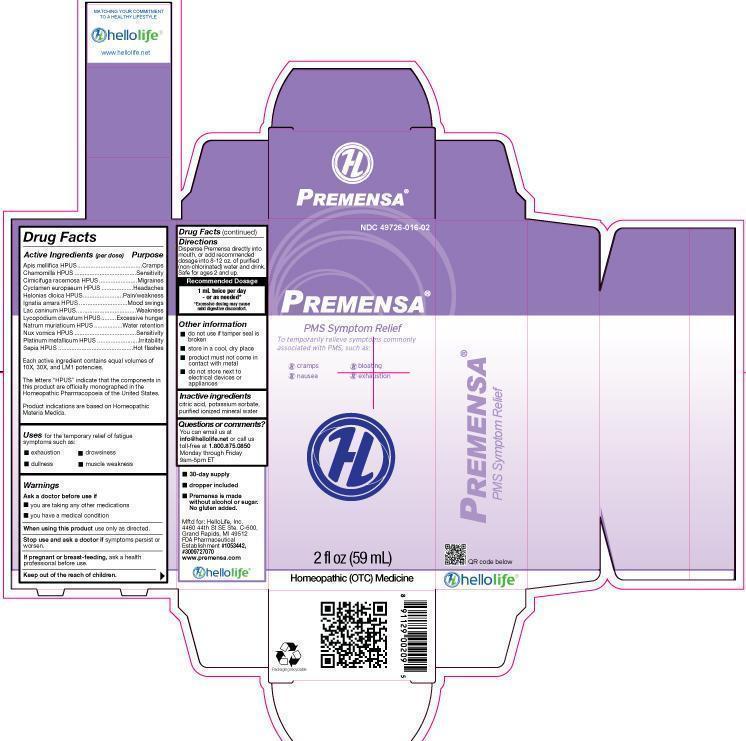 DRUG LABEL: Premensa
NDC: 49726-016 | Form: LIQUID
Manufacturer: Hello Life, Inc.
Category: homeopathic | Type: HUMAN OTC DRUG LABEL
Date: 20181226

ACTIVE INGREDIENTS: APIS MELLIFERA 10 [hp_X]/59 mL; CHAMOMILE 10 [hp_X]/59 mL; BLACK COHOSH 10 [hp_X]/59 mL; CYCLAMEN PURPURASCENS TUBER 10 [hp_X]/59 mL; CHAMAELIRIUM LUTEUM ROOT 10 [hp_X]/59 mL; STRYCHNOS IGNATII SEED 10 [hp_X]/59 mL; CANIS LUPUS FAMILIARIS MILK 10 [hp_X]/59 mL; LYCOPODIUM CLAVATUM SPORE 10 [hp_X]/59 mL; SODIUM CHLORIDE 10 [hp_X]/59 mL; STRYCHNOS NUX-VOMICA SEED 10 [hp_X]/59 mL; PLATINUM 10 [hp_X]/59 mL; SEPIA OFFICINALIS JUICE 10 [hp_X]/59 mL
INACTIVE INGREDIENTS: WATER; POTASSIUM SORBATE; CITRIC ACID MONOHYDRATE

Drug Facts

Active Ingredients (per dose)

Apis mellifica HPUS
Chamomilla HPUS
Cimicifuga racemosa HPUS
Cyclamen europaeum HPUS
Helonias dioica HPUS
Ignatia amara HPUS
Lac caninum HPUS
Lycopodium clavatum HPUS
Natrum muriaticum HPUS
Nux vomica HPUS
Platinum metallicum HPUS
Sepia HPUS
Each active ingredient contains equal volumes of 10X, 30X, and LM1 potencies. The letters “HPUS” indicate that the components in this product are officially monographed in the Homeopathic Pharmacopoeia of the United States. Product indications are based on Homeopathic Materia Medica. Product indications are based on Homeopathic Materia Medica.

Purpose

Apis mellifica HPUS..…………………………Cramps
Chamomilla HPUS…………………………….Sensitivity
Cimicifuga racemosa HPUS.……………......Migraines
Cyclamen europaeum HPUS………….….....Headaches
Helonias dioica HPUS………………………..Pain/weakness
Ignatia amara HPUS.…………………..……..Mood swings
Lac caninum HPUS.…………………………..Weakness
Lycopodium clavatum HPUS..…..……….....Excessive hunger
Natrum muriaticum HPUS…………………....Water retention
Nux vomica HPUS…………………………….Sensitivity
Platinum metallicum HPUS……………….....Irritability
Sepia HPUS……………..……………………..Hot flashes

Uses

to temporarily relieve symptoms commonly associated with PMS, such as:

- exhaustion
- dullness
- drowsiness
- muscle weakness

Warnings

Ask a doctor before use if

- you are taking any other medications
- you have a medical condition

When using this product use only as directed.

Stop use and ask a doctor if symptoms persist or worsen.

PREGNANCY OR BREAST FEEDING

If pregnant or breast-feeding, ask a health professional before use.

Keep out of the reach of children.

Directions

Dispense Premensa directly into mouth, or add recommended dosage into 8-12 oz purified (non-chlorinated) water and drink. Safe for ages 2 and up.

RECOMMENDED DOSAGE

1 mL twice per day
-or as needed*

*Excessive dosing may cause mild digestive discomfort.

Other information

- do not use if tamper seal is broken
- store in a cool, dry place
- product must not come in contact with metal
- do not store next to electrical devices or appliances

Inactive Ingredients

citric acid, potassium sorbate, purified ionized mineral water.

Questions or comments?

You can email us at info@hellolife.net or call us toll-free at 1.800.875.0850 Monday through Friday, 9am-5pm ET.

DESCRIPTION

- 30-day supply
- dropper included
- Premensa is made without alcohol or sugar; no gluten added.

Mftd for: HelloLife, Inc.
4460 44th St. SE, Ste. C-600
Grand Rapids, MI 49512
FDA Pharmaceutical Establishment #1053442, #3009727070
www.premensa.com

Principal Display Panel

NDC 49726-016-02

PREMENSA®

PMS Symptom Relief

To temporarily relieve symptoms commonly associated with PMS, such as:

- cramps
- nausea
- bloating
- exhaustion

2 fl. oz (59 mL)

Homeopathic (OTC) Medicine